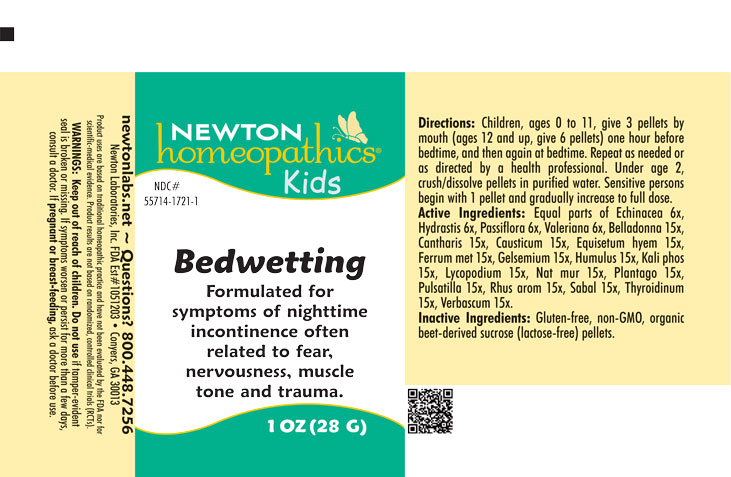 DRUG LABEL: Bedwetting
NDC: 55714-1721 | Form: PELLET
Manufacturer: Newton Laboratories, Inc.
Category: homeopathic | Type: HUMAN OTC DRUG LABEL
Date: 20250724

ACTIVE INGREDIENTS: ECHINACEA, UNSPECIFIED 6 [hp_X]/1 g; VALERIAN 6 [hp_X]/1 g; ATROPA BELLADONNA 15 [hp_X]/1 g; LYTTA VESICATORIA 15 [hp_X]/1 g; CAUSTICUM 15 [hp_X]/1 g; EQUISETUM HYEMALE 15 [hp_X]/1 g; IRON 15 [hp_X]/1 g; GELSEMIUM SEMPERVIRENS ROOT 15 [hp_X]/1 g; HOPS 15 [hp_X]/1 g; DIBASIC POTASSIUM PHOSPHATE 15 [hp_X]/1 g; GOLDENSEAL 6 [hp_X]/1 g; SODIUM CHLORIDE 15 [hp_X]/1 g; PLANTAGO MAJOR 15 [hp_X]/1 g; ANEMONE PULSATILLA 15 [hp_X]/1 g; TOXICODENDRON PUBESCENS LEAF 15 [hp_X]/1 g; SAW PALMETTO 15 [hp_X]/1 g; THYROID, UNSPECIFIED 15 [hp_X]/1 g; VERBASCUM THAPSUS 15 [hp_X]/1 g; PASSIFLORA INCARNATA FLOWERING TOP 6 [hp_X]/1 g; LYCOPODIUM CLAVATUM SPORE 15 [hp_X]/1 g
INACTIVE INGREDIENTS: SUCROSE

Bedwetting 1721P

INDICATIONS & USAGE SECTION

Formulated for symptoms of nighttime incontinence often related to fear, nervousness, muscle tone and trauma.

OTC - ACTIVE INGREDIENT SECTION

Equal parts of Echinacea 6x, Hydrastis canadensis 6x, Passiflora incarnata 6x, Valeriana officinalis 6x, Belladonna 15x, Cantharis 15x, Causticum 15x, Equisetum hyemale 15x, Ferrum metallicum 15x, Gelsemium sempervirens 15x, Humulus lupulus 15x, Kali phosphoricum 15x, Lycopodium clavatum 15x, Natrum muriaticum 15x, Plantago major 15x, Pulsatilla 15x, Rhus aromatica 15x, Sabal serrulata 15x, Thyroidinum 15x, Verbascum thapsus 15x.

OTC - PURPOSE SECTION

Formulated for associated symptoms often related to fear, nervousness, muscle tone and trauma.

INACTIVE INGREDIENT SECTION

Gluten-free, non-GMO, organic beet-derived sucrose (lactose-free) pellets

QUESTIONS SECTION

newtonlabs.net – Questions? 800.448.7256

Newton Laboratories, Inc. FDA Est # 1051203 - Conyers, GA 30013

WARNINGS SECTION

WARNINGS: Keep out of reach of children. Do not use if tamper-evident seal is broken or missing. If symptoms worsen or persist for more than a few days, consult a doctor. If pregnant or breast-feeding, ask a doctor before use.

OTC - PREGNANCY OR BREAST FEEDING SECTION

If pregnant or breast-feeding, ask a doctor before use.

OTC - KEEP OUT OF REACH OF CHILDREN SECTION

Keep out of reach of children.

DOSAGE & ADMINISTRATION SECTION

Directions: Children, ages 0 to 11, give 3 pellets by mouth (ages 12 and up, give 6 pellets) one hour before bedtime, and then again at bedtime. Repeat as needed or as directed by a health professioal. Under age 2, crush/dissolve pellets in purified water. Sensitive person begin with 1 pellet and gradually increase to full dose.